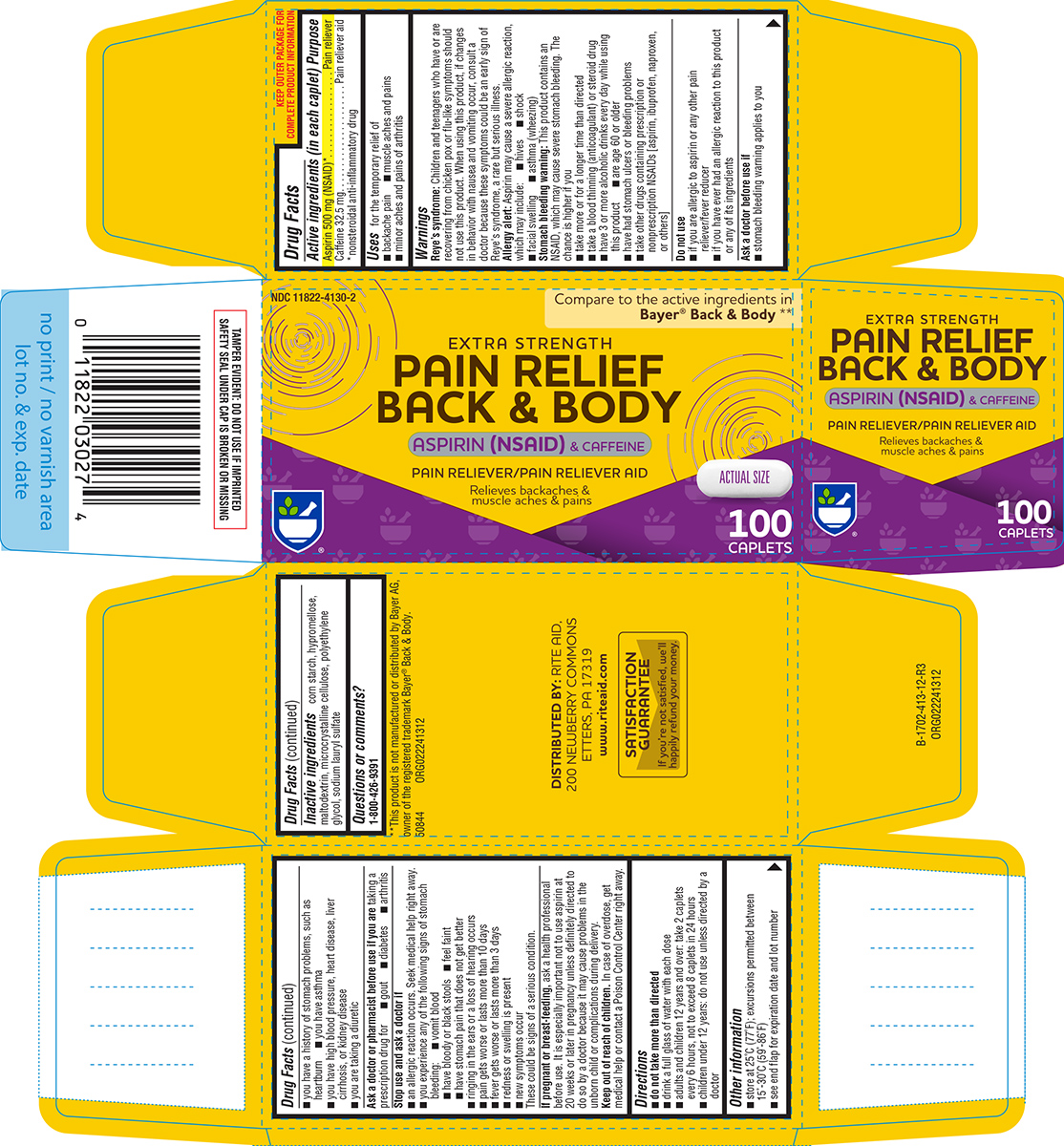 DRUG LABEL: pain relief back and body
NDC: 11822-4130 | Form: TABLET, FILM COATED
Manufacturer: Rite Aid Corporation
Category: otc | Type: HUMAN OTC DRUG LABEL
Date: 20260107

ACTIVE INGREDIENTS: ASPIRIN 500 mg/1 1; CAFFEINE 32.5 mg/1 1
INACTIVE INGREDIENTS: STARCH, CORN; HYPROMELLOSE, UNSPECIFIED; MALTODEXTRIN; MICROCRYSTALLINE CELLULOSE; POLYETHYLENE GLYCOL, UNSPECIFIED; SODIUM LAURYL SULFATE

Rite Aid 44-413

Active ingredients (in each caplet)

Aspirin 500 mg (NSAID)*
Caffeine 32.5 mg
*nonsteroidal anti-inflammatory drug

Purpose

Pain reliever
Pain reliever aid

Uses

for the temporary relief of:

- backache pain
- muscle aches and pains
- minor aches and pains of arthritis

Warnings

Reye's syndrome: Children and teenagers who have or are recovering from chicken pox or flu-like symptoms should not use this product. When using this product, if changes in behavior with nausea and vomiting occur, consult a doctor because these symptoms could be an early sign of Reye's syndrome, a rare but serious illness.

Allergy alert: Aspirin may cause a severe allergic reaction, which may include:

- hives
- facial swelling
- shock
- asthma (wheezing)

Stomach bleeding warning: This product contains an NSAID, which may cause severe stomach bleeding. The chance is higher if you:

- take more or for a longer time than directed
- take a blood thinning (anticoagulant) or steroid drug
- are age 60 or older
- take other drugs containing prescription or nonprescription NSAIDs [aspirin, ibuprofen, naproxen, or others]
- have 3 or more alcoholic drinks every day while using this product
- have had stomach ulcers or bleeding problems

Do not use

- if you are allergic to aspirin or any other pain reliever/fever reducer
- if you have ever had an allergic reaction to this product or any of its ingredients

Ask a doctor before use if

- stomach bleeding warning applies to you
- you have a history of stomach problems, such as heartburn
- you have high blood pressure, heart disease, liver cirrhosis, or kidney disease
- you have asthma
- you are taking a diuretic

Ask a doctor or pharmacist before use if you are

taking a prescription drug for

- gout
- diabetes
- arthritis

Stop use and ask a doctor if

- an allergic reaction occurs. Seek medical help right away.
- you experience any of the following signs of stomach bleeding:
  - vomit blood
  - have bloody or black stools
  - feel faint
  - have stomach pain that does not get better
- ringing in the ears or a loss of hearing occurs
- pain gets worse or lasts more than 10 days
- fever gets worse or lasts more than 3 days
- redness or swelling is present
- new symptoms occur

These could be signs of a serious condition.

If pregnant or breast-feeding,

ask a health professional before use. It is especially important not to use aspirin at 20 weeks or later in pregnancy unless definitely directed to do so by a doctor because it may cause problems in the unborn child or complications during delivery.

Keep out of reach of children.

In case of overdose, get medical help or contact a Poison Control Center right away.

Directions

- do not take more than directed
- drink a full glass of water with each dose
- adults and children 12 years and over: take 2 caplets every 6 hours, not to exceed 8 caplets in 24 hours
- children under 12 years: do not use unless directed by a doctor

Other information

- store at 25ºC (77ºF); excursions permitted between 15º-30ºC (59º-86ºF)
- see end flap for expiration date and lot number

Inactive ingredients

corn starch, hypromellose, maltodextrin, microcrystalline cellulose, polyethylene glycol, sodium lauryl sulfate

Questions or Comments?

1-800-426-9391

Principal display panel

NDC 11822-4130-2

Compare to the active ingredients in
Bayer® Back & Body**

EXTRA STRENGTH
PAIN RELIEF
BACK & BODY

ASPIRIN (NSAID) & CAFFEINE
PAIN RELIEVER/PAIN RELIEVER AID

Relieves backaches &
muscle aches & pains

ACTUAL SIZE

100
CAPLETS

TAMPER EVIDENT: DO NOT USE IF IMPRINTED
SAFETY SEAL UNDER CAP IS BROKEN OR MISSING

**This product is not manufactured or distributed by Bayer AG,
owner of the registered trademark Bayer® Back & Body.

50844 ORG022241312

DISTRIBUTED BY: RITE AID,
200 NEWBERRY COMMONS
ETTER, PA 17319
www.riteaid.com

SATISFACTION
GUARANTEE
If you're not satisfied, we'll
happily refund your money.

Rite Aid 44-413